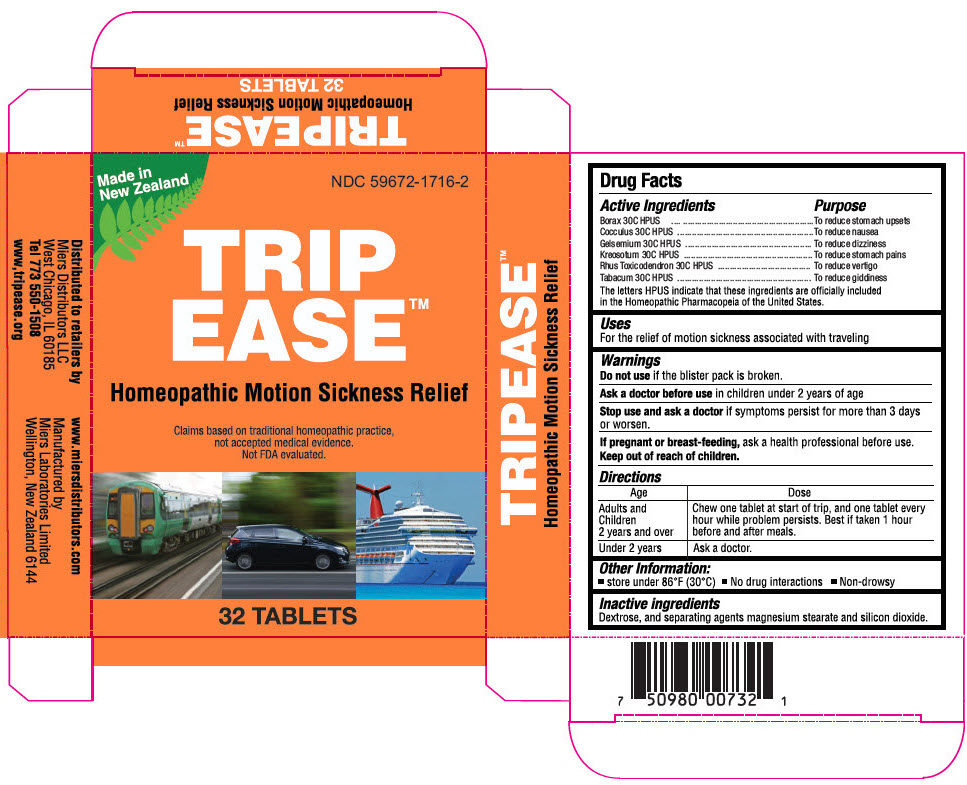 DRUG LABEL: TRIP EASE
NDC: 59672-1716 | Form: TABLET
Manufacturer: Miers Laboratories
Category: homeopathic | Type: HUMAN OTC DRUG LABEL
Date: 20230920

ACTIVE INGREDIENTS: SODIUM BORATE 30 [hp_C]/1 1; ANAMIRTA COCCULUS SEED 30 [hp_C]/1 1; GELSEMIUM SEMPERVIRENS ROOT 30 [hp_C]/1 1; WOOD CREOSOTE 30 [hp_C]/1 1; TOXICODENDRON PUBESCENS LEAF 30 [hp_C]/1 1; TOBACCO LEAF 30 [hp_C]/1 1
INACTIVE INGREDIENTS: DEXTROSE, UNSPECIFIED FORM 242 mg/1 1; SILICON DIOXIDE; MAGNESIUM STEARATE

TRIP EASE™

Drug Facts

ACTIVE INGREDIENT

Active Ingredients | Purpose
Borax 30C HPUS | To reduce stomach upsets
Cocculus 30C HPUS | To reduce nausea
Gelsemium 30C HPUS | To reduce dizziness
Kreosotum 30C HPUS | To reduce stomach pains
Rhus Toxicodendron 30C HPUS | To reduce vertigo
Tabacum 30C HPUS | To reduce giddiness
The letters HPUS indicate that these ingredients are officially included in the Homeopathic Pharmacopeia of the United States.

Uses

For the relief of motion sickness associated with traveling

Warnings

Do not use if the blister pack is broken.

Ask a doctor before use in children under 2 years of age

Stop use and ask a doctor if symptoms persist for more than 3 days or worsen.

PREGNANCY OR BREAST FEEDING

If pregnant or breast-feeding, ask a health professional before use.

Keep out of reach of children.

Directions

Age | Dose
Adults and Children 2 years and over | Chew one tablet at start of trip, and one tablet every hour while problem persists. Best taken 1 hour before and after meals.
Under 2 years | Ask a doctor.

Other Information

- store under 85°F (30°C)
- No drug interactions
- Non drowsy

Inactive ingredients

Dextrose, and separating agents magnesium stearate and silicon dioxide.

Distributed to retailers by
Miers Distributors LLC
West Chicago, IL 60185

Manufactured by
Miers Laboratories Limited
Wellington New Zealand 6144

PRINCIPAL DISPLAY PANEL - 32 Tablet Blister Pack Carton

Made in
New Zealand

NDC 59672-1716-2

TRIP
EASE™

Homeopathic Motion Sickness Relief

Claims based on traditional homeopathic practice,
not accepted medical evidence.
Not FDA evaluated.

32 TABLETS